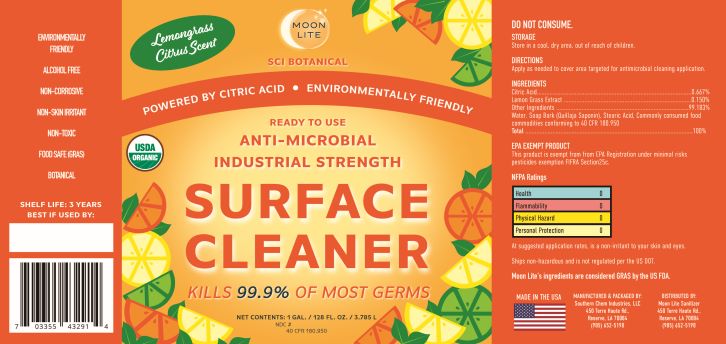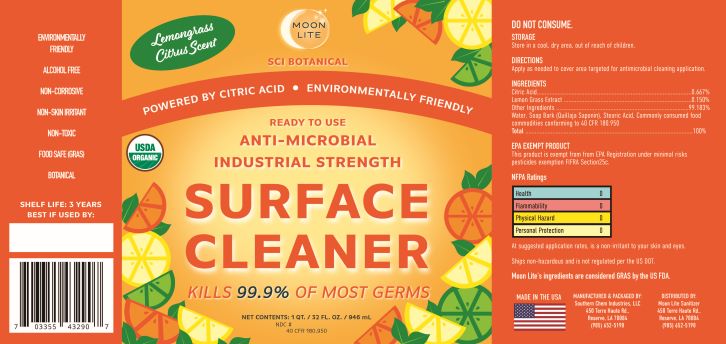 DRUG LABEL: Surface Cleaner
NDC: 55549-201 | Form: LIQUID
Manufacturer: Southern Chem Industries LLC
Category: otc | Type: HUMAN OTC DRUG LABEL
Date: 20210222

ACTIVE INGREDIENTS: CITRIC ACID MONOHYDRATE 5.6 mg/100 mL
INACTIVE INGREDIENTS: JAMMU LEMONGRASS OIL 1 mL/100 mL; WATER; QUILLAJA SAPONARIA BARK 0.03 mg/100 mL; STEARIC ACID 1 mL/100 mL

Citric Acid

1. Citric Acid
2. Lemon Grass Extract
3. Water
4. Quillaja Saponin (Soap Bark)
5. Stearic Acid

Active Ingredient(s)

Citric Acid

Purpose

Surface Cleaner

Use

For surface cleaning to decrease bacteria.

Warnings

DO NOT CONSUME

Keep out of reach of children. If swallowed, get medical help or contact a Poison Control Center right away.

Other information

Store in a cool, dry area, out of reach of children

Inactive ingredients

Lemon Grass Estract, Water, Soap Bark (Quillaja Saponin), Stearic Acid.

EPA Excempt Product

This Product is excempt from the EPA Registration under minimal risk pesticide exception FIFRA Section 25c

Directions

Apply as needed to cover area targeted for antimicrobial cleansing application.